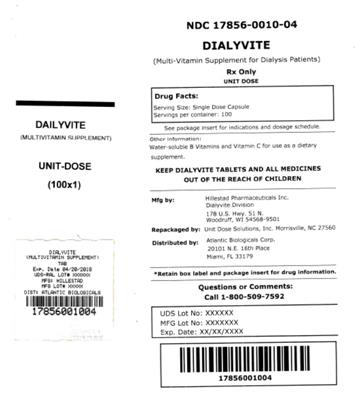 DRUG LABEL: Dialyvite
NDC: 17856-0010 | Form: TABLET, COATED
Manufacturer: Atlantic Biologicals Corps
Category: prescription | Type: HUMAN PRESCRIPTION DRUG LABEL
Date: 20170511

ACTIVE INGREDIENTS: ASCORBIC ACID 100 mg/1 1; THIAMINE MONONITRATE 1.5 mg/1 1; RIBOFLAVIN 1.7 mg/1 1; NIACINAMIDE 20 mg/1 1; PYRIDOXINE HYDROCHLORIDE 10 mg/1 1; FOLIC ACID 1 mg/1 1; COBALAMIN 6 ug/1 1; BIOTIN 300 ug/1 1; CALCIUM PANTOTHENATE 10 mg/1 1
INACTIVE INGREDIENTS: MICROCRYSTALLINE CELLULOSE; Croscarmellose Sodium; Glyceryl Monostearate; Starch, Corn; HYPROMELLOSE, UNSPECIFIED; POLYETHYLENE GLYCOL, UNSPECIFIED; Calcium Stearate; Cochineal

Dialyvite

DESCRIPTION

Dialyvite is a prescription folic acid supplement with additional nutrients for kidney dialysis patients. Dialyvite is a small, round, light pink, clear-coated tablet, with debossed "H" on one side.

Each tablet contains:

Folic Acid.....1 mg

Vitamin C (Ascorbic Acid).....100 mg

Thiamine (Thiamine Mononitrate).....1.5 mg

Riboflavin.....1.7 mg

Niacinamide.....20 mg

Vitamin B6 (Pyridoxine HCl).....10 mg

Vitamin B12 (Methylcobalamin).....6 mcg

Biotin.....300 mcg

Pantothenic Acid (Calcium Pantothenate).....10 mg

Inactive ingredients:

Microcrystalline Cellulose, Croscarmellose Sodium, Mono- and Diglycerides, Starch, Hypromellose, Polyethylene Glycol, Calcium Stearate, Carmine (color).

INDICATIONS AND USAGE

Dialyvite is a prescription folic acid supplement with additional nutrients indicated for use in improving the nutritional status of renal dialysis patients.

CONTRAINDICATIONS

This product is contraindicated in patients with known hypersensitivity to any of the ingredients.

PRECAUTIONS

Folic acid supplementation may obscure pernicious anemia, in that hematologic remission can occur while neurological manifestations progress.

Keep out of reach of children.

ADVERSE REACTIONS

Allergic sensitizations have been reported following oral administration of folic acid.

Consult your physician immediately if adverse side effects occur.

DOSAGE AND ADMINISTRATION

Take one tablet per day or as directed by your physician, orally.

HOW SUPPLIED

Product: 17856-0010

NDC: 17856-0010-4 1 TABLET, COATED in a DOSE PACK